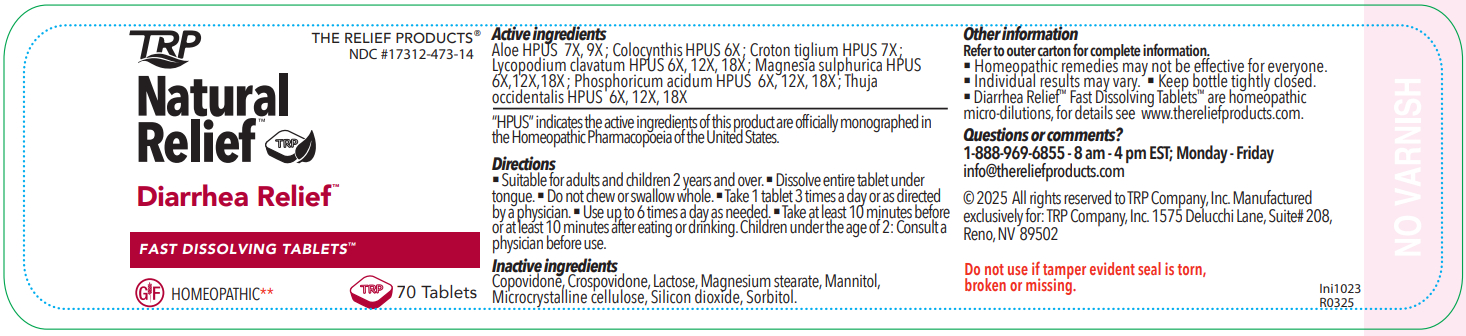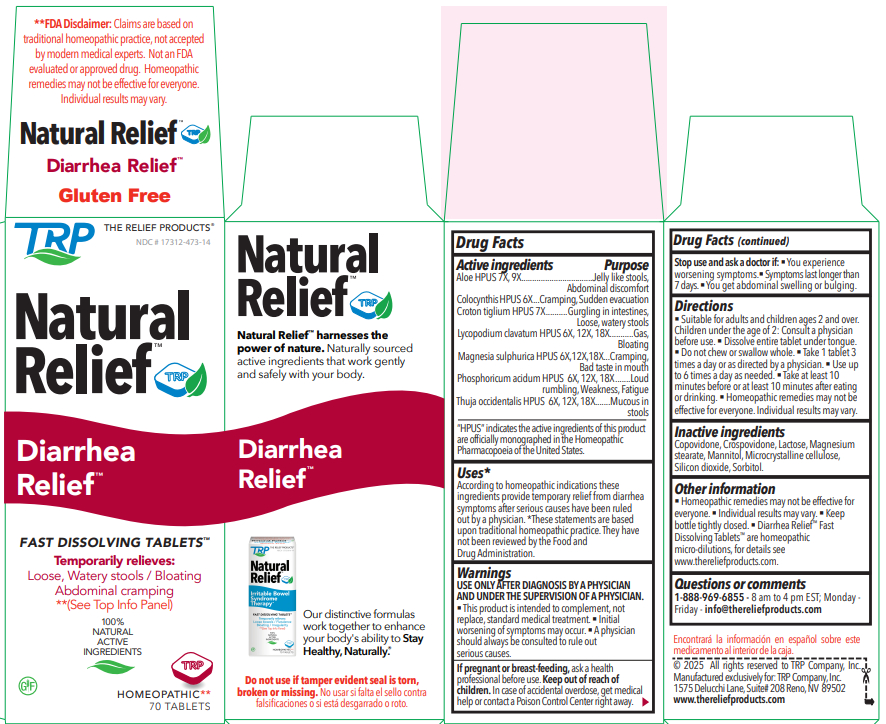 DRUG LABEL: Natural Relief Diarrhea Relief
NDC: 17312-473 | Form: TABLET, ORALLY DISINTEGRATING
Manufacturer: TRP Company
Category: homeopathic | Type: HUMAN OTC DRUG LABEL
Date: 20251112

ACTIVE INGREDIENTS: THUJA OCCIDENTALIS LEAFY TWIG 6 [hp_X]/1 1; PHOSPHORIC ACID 6 [hp_X]/1 1; MAGNESIUM SULFATE HEPTAHYDRATE 6 [hp_X]/1 1; LYCOPODIUM CLAVATUM SPORE 6 [hp_X]/1 1; CROTON TIGLIUM SEED 7 [hp_X]/1 1; CITRULLUS COLOCYNTHIS FRUIT PULP 6 [hp_X]/1 1; ALOE 7 [hp_X]/1 1
INACTIVE INGREDIENTS: MANNITOL; SORBITOL; CROSPOVIDONE; CELLULOSE, MICROCRYSTALLINE; COPOVIDONE; SILICON DIOXIDE; LACTOSE; MAGNESIUM STEARATE

Natural Relief Diarrhea Relief

Active ingredients

Aloe 7X, 9X

Colocynthis 6X

Croton tiglium 7X

Lycopodium clavatum 6X, 12X, 18X

Magnesia sulphurica 6X, 12X, 18X

Phosphoricum acidum 6X, 12X, 18X

Thuja occidentalis 6X, 12X, 18X

Purpose

Aloe - Jelly like stools, Abdominal discomfort

Colocynthis - Cramping , Sudden evacuation

Croton tiglium - Gurgling in intestines, Loose, watery stools

Lycopodium clavatum - Gas, Bloating

Magnesia sulphurica - Cramping, Bad taste in mouth

Phosphoricum acidum - Loud rumbling, Weakness, Fatigue

Thuja occidentalis - Mucous in stools

Uses*

According to homeopathic indications these ingredients provide temporary relief from diarrhea symptoms after serious causes have been ruled out by a physician.

*These statements are based upon traditional homeopathic practice. They have not been reviewed by the Food and Drug Administration.

Warnings

USE ONLY AFTER DIAGNOSIS BY A PHYSICIAN AND UNDER THE SUPERVISION OF A PHYSICIAN.

- This product is intended to complement, not replace, standard medical treatment.
- Initial worsening of symptoms may occur.
- A physician should always be consulted to rule out serious causes.

PREGNANCY OR BREAST FEEDING

If pregnant or breast-feeding, ask a health professional before use.

Keep out of reach of children. In case of accidental overdose, get medical help or contact a Poison Control Center right away.

Stop use and ask a doctor if:

- You experience worsening symptoms.
- Symptoms last longer than 7 days.
- You get abdominal swelling or bulging.

Directions

- Suitable for adults and children ages 2 and over. Children under the age of 2: Consult a physician before use.
- Dissolve entire tablet under tongue.
- Do not chew or swallow whole.
- Take 1 tablet 3 times a day or as directed by a physician.
- Use up to 6 times a day as needed.
- Take at least 10 minutes before or at least 10 minutes after eating or drinking.
- Homeopathic remedies may not be effective for everyone. Individual results may vary.

Inactive ingredients

Copovidone, Crospovidone, Lactose, Magnesium stearate, Mannitol, Microcrystalline cellulose, Silicon dioxide, Sorbitol.

Other information

- Homeopathic remedies may not be effective for everyone.
- Individual results may vary.
- Keep bottle tightly closed.
- Diarrhea Relief™ Fast Dissolving Tablets ™ are homeopathic micro-dilutions, for details see www.thereliefproducts.com .

Questions or comments

1-888-969-6855 - 8 am to 4 pm EST; Monday - Friday - info@thereliefproducts.com

Do not use if tamper evident seal is torn, broken or missing.